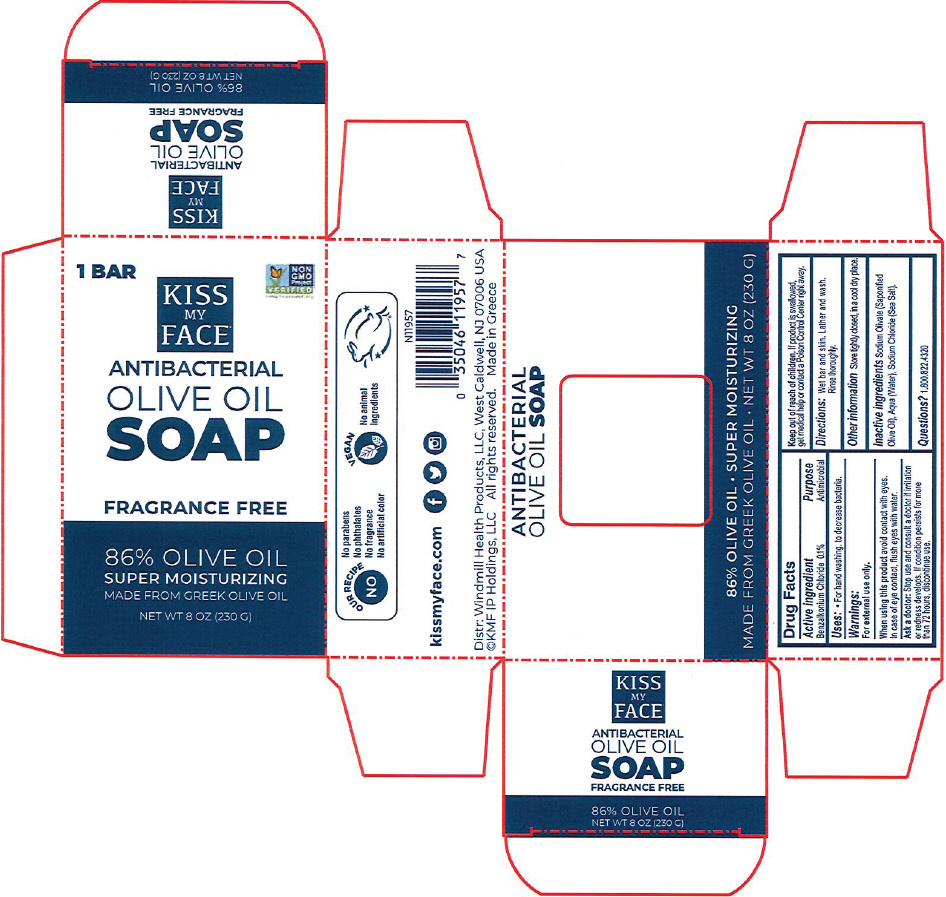 DRUG LABEL: Kiss My Face Antibacterial Olive Bar Fragrance-Free
NDC: 74154-011 | Form: SOAP
Manufacturer: Windmill Health Products, LLC 
Category: otc | Type: HUMAN OTC DRUG LABEL
Date: 20210125

ACTIVE INGREDIENTS: BENZALKONIUM CHLORIDE 0.1 g/100 g
INACTIVE INGREDIENTS: WATER; SEA SALT

Kiss My Face® Antibacterial Olive Oil Bar Soap Fragrance-Free

Drug Facts

Active Ingredient

Benzalkonium Chloride 0.1%

Purpose

Antimicrobial

Uses

For hand washing, to decrease bacteria

Warnings

For external use only.

When using this product avoid contact with eyes. In case of contact, flush eyes with water.

Ask a doctor

Stop use and consult a doctor if irritation or redness develops. If condition persists for more than 72 hours, discontinue use.

Keep out of reach of children. If product is swallowed, get medical help or contact a Poison Control Center right away.

Directions

Wet bar and skin. Lather and wash. Rinse thoroughly.

Other information

Store tightly closed, in a cool dry place.

Inactive Ingredients

Sodium olivate (Saponified Olive Oil), Aqua (Water), Sodium Chloride (Sea Salt).

Questions?

1.800.822.4320

PRINCIPAL DISPLAY PANEL - 230 G Applicator Carton

1 BAR

NON
GMO
Project
VERIFIED
nongmoproject.org

KISS
MY
FACE

ANTIBACTERIAL
OLIVE OIL
SOAP

FRAGRANCE FREE

86% OLIVE OIL
SUPER MOISTURIZING
MADE FROM GREEK OLIVE OIL

NET WT 8 OZ (230 G)